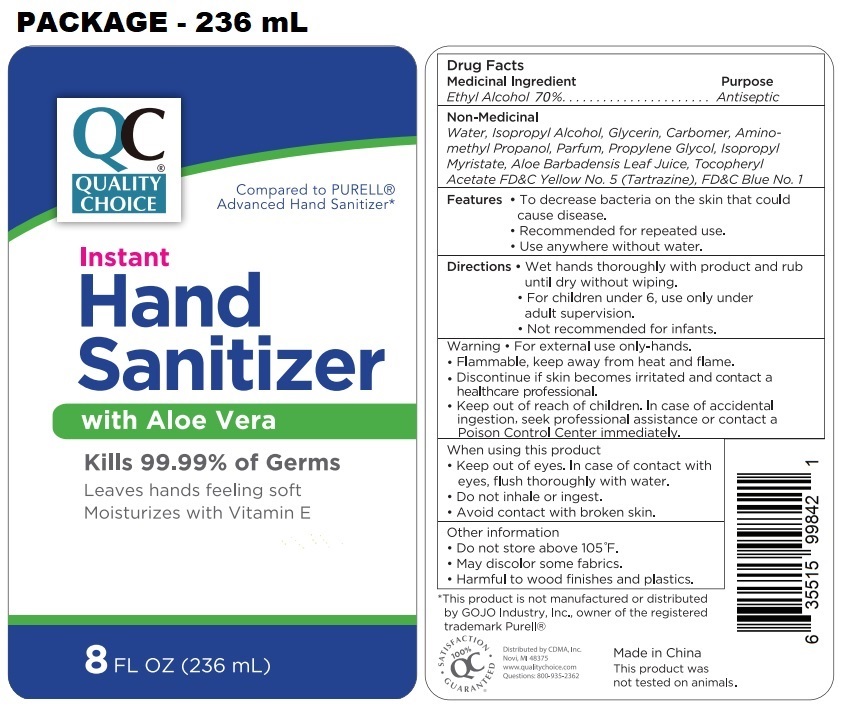 DRUG LABEL: QUALITY CHOICE INSTANT HAND SANITIZER
NDC: 77725-004 | Form: GEL
Manufacturer: L.e.d. Cosmetics, Inc.
Category: otc | Type: HUMAN OTC DRUG LABEL
Date: 20241210

ACTIVE INGREDIENTS: ALCOHOL 70 mL/100 mL
INACTIVE INGREDIENTS: WATER; ISOPROPYL ALCOHOL; GLYCERIN; CARBOMER HOMOPOLYMER, UNSPECIFIED TYPE; AMINOMETHYLPROPANOL; PROPYLENE GLYCOL; ISOPROPYL MYRISTATE; ALOE VERA LEAF; .ALPHA.-TOCOPHEROL ACETATE; FD&C YELLOW NO. 5; FD&C BLUE NO. 1

QUALITY CHOICE® Instant Hand Sanitizer with Aloe Vera

Medicinal Ingredient

Ethyl Alcohol 70%

Purpose

Antiseptic

Non-Medicinal

Water, Isopropyl Alcohol, Glycerin, Carbomer, Aminomethyl Propanol, Parfum, Propylene Glycol, Isopropyl Myristate, Aloe Barbadensis Leaf Juice, Tocopheryl Acetate, FD&C Yellow No. 5 (Tartrazine), FD&C Blue No.1

Features

• To decrease bacteria on the skin that could cause disease.

• Recommended for repeated use.

• Use anywhere without water.

Directions

• Wet hands thoroughly with product and rub until dry without wiping.

• For children under 6, use only under adult supervision.

• Not recommended for infants.

Warning

• For external use only-hands.

• Flammable, keep away from heat and flame.

• Discontinue if skin becomes irritated and contact a healthcare professional.

When using this product

• Keep out of eyes. In case of contact with eyes, flush thoroughly with water.

• Do not inhale or ingest.

• Avoid contact with broken skin.

• Keep out of reach of children. In case of accidental ingestion, seek professional assistance or contact a Poison Control Center immediately.

Other information

• Do not store above 105°F.

• May discolor some fabrics.

• Harmful to wood finishes and plastics.

Compared to PURELL® Advanced Hand Sanitizer*

with Aloe Vera

Kills 99.99% of Germs

Leaves hands feeling soft

Moisturizes with vitamin E

*This product is not manufactured or distributed by GOJO Industry, Inc., owner of the registered trademark Purell®

SATISFACTION 100% QC GUARANTEED

Distributed by CDMA, Inc.

43157 W 9 Mile Rd

Novi, MI 48375

www.qualitychoice.com

Questions: 800-935-2362

Made in China

This product was not tested on animals.